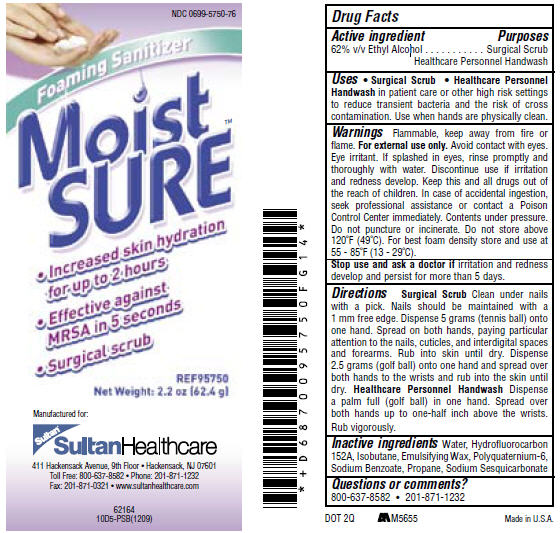 DRUG LABEL: Moist SURE
NDC: 0699-5720 | Form: LIQUID
Manufacturer: DSHealthcare
Category: otc | Type: HUMAN OTC DRUG LABEL
Date: 20100209

ACTIVE INGREDIENTS: Triclosan 7.5 mg/1 g
INACTIVE INGREDIENTS: Water; Hexylene Glycol; Sorbitol; ETHANOLAMINE; CITRIC ACID MONOHYDRATE; AMMONIUM LAURYL SULFATE

Moist SURE™ Foaming Sanitizer

Drug Facts

Active ingredient

62% v/v Ethyl Alcohol

Purposes

Surgical Scrub

Healthcare Personnel Handwash

Uses

- Surgical Scrub
- Healthcare Personnel Handwash in patient care or other high risk settings to reduce transient bacteria and the risk of cross contamination. Use when hands are physically clean.

Warnings

Flammable, keep away from fire or flame. For external use only. Avoid contact with eyes. Eye irritant. If splashed in eyes, rinse promptly and thoroughly with water. Discontinue use if irritation and redness develop. Keep this and all drugs out of the reach of children. In case of accidental ingestion, seek professional assistance or contact a Poison Control Center immediately. Contents under pressure. Do not puncture or incinerate. Do not store above 120°F (49°C). For best foam density store and use at 55 - 85°F (13 - 29°C).

Stop use and ask a doctor if irritation and redness develop and persist for more than 5 days.

Directions

Surgical Scrub Clean under nails with a pick. Nails should be maintained with a 1 mm free edge. Dispense 5 grams (tennis ball) onto one hand. Spread on both hands, paying particular attention to the nails, cuticles, and interdigital spaces and forearms. Rub into skin until dry. Dispense 2.5 grams (golf ball) onto one hand and spread over both hands to the wrists and rub into the skin until dry. Healthcare Personnel Handwash Dispense a palm full (golf ball) in one hand. Spread over both hands up to one-half inch above the wrists. Rub vigorously.

Inactive ingredients

Water, Hydrofluorocarbon 152A, Isobutane, Emulsifying Wax, Polyquaternium-6, Sodium Benzoate, Propane, Sodium Sesquicarbonate

Questions or comments?

800-637-8582 • 201-871-1232

PRINCIPAL DISPLAY PANEL - 62.4 g Label

NDC 0699-5750-76

Foaming Sanitizer

Moist
SURE™

- Increased skin hydration
  for up to 2 hours
- Effective against
  MRSA in 5 seconds
- Surgical scrub

REF95750
Net Weight: 2.2 oz [62.4 g]

Manufactured for:

Sultan®

Sultan Healthcare

411 Hackensack Avenue, 9th Floor • Hackensack, NJ 07601
Toll Free: 800-637-8582 • Phone: 201-871-1232
Fax: 201-871-0321 • www.sultanhealthcare.com

62164
10D5-PSB(1209)